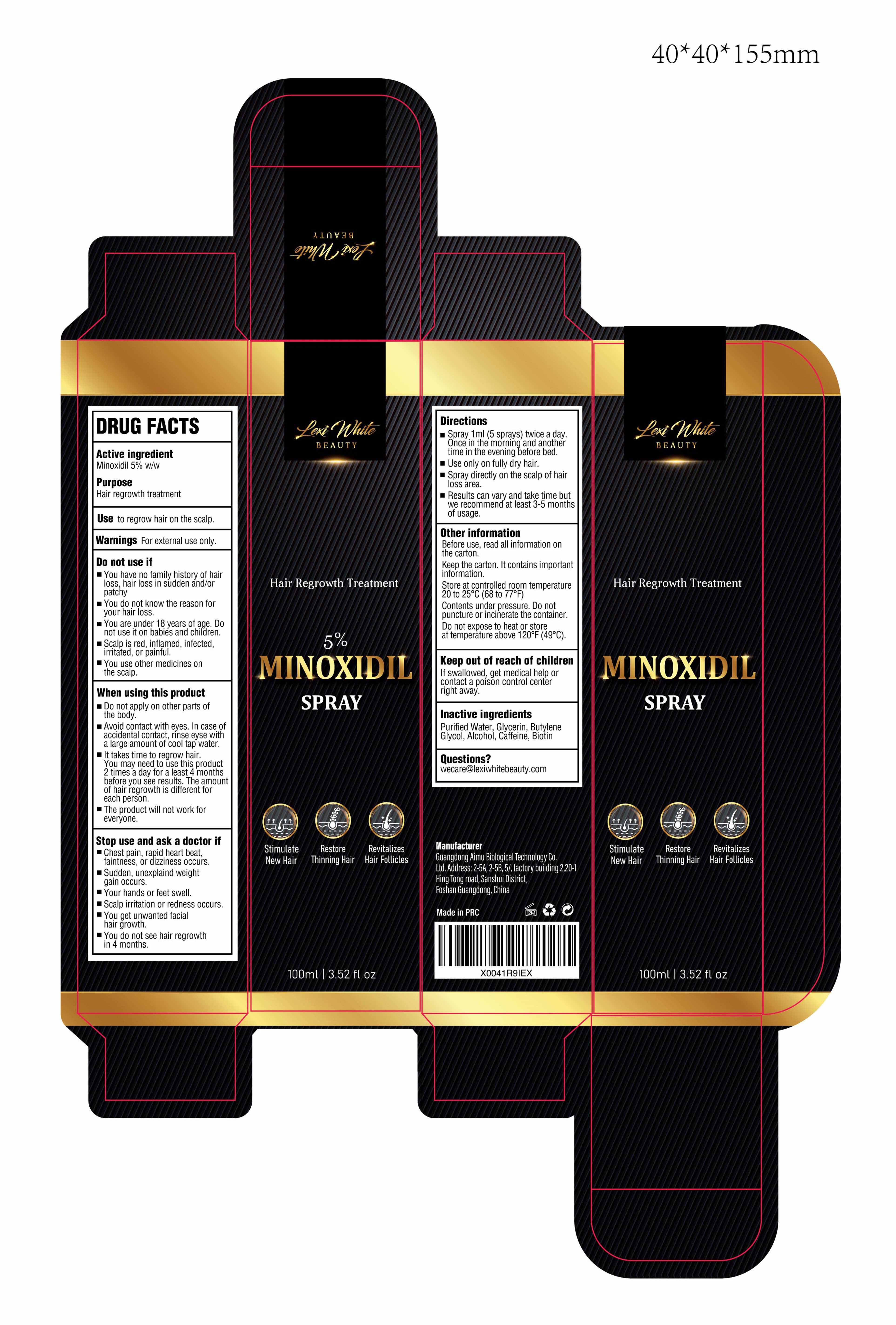 DRUG LABEL: Lexi White Beauty Hair Regrowth 5% MinoxidilSpray
NDC: 83566-403 | Form: LIQUID
Manufacturer: Guangdong Aimu Biological Technology Co., Ltd
Category: otc | Type: HUMAN OTC DRUG LABEL
Date: 20240415

ACTIVE INGREDIENTS: MINOXIDIL 0.05 g/1 mL
INACTIVE INGREDIENTS: ALCOHOL; WATER; CAFFEINE; GLYCERIN; BUTYLENE GLYCOL; BIOTIN

Lexi White Beauty Hair Regrowth 5% Minoxidil Spray

Lexi White Beauty Hair Regrowth 5% Minoxidil Spray

ACTIVE INGREDIENT

Minoxidil 5%

PURPOSE

Hair regrowth treatment

INDICATIONS AND USAGE

Use to regrow hair on the scalp

WARNINGS

For external use only

DO NOT USE

You have no family history of hair loss, hair loss in sudden and/or patchy.
You do not know the reason for your hair loss.
You are under 18 years of age. Do not use it on babies and children.
Scalp is red, inflamed, infected, irritated, or painful.
You use other medicines on the scalp.

WHEN USING

Do not apply on other parts of the body.

Avoid contact with eyes. ln case of accidental contact, rinse eyse with a large amount of cool tap water.

lt takes time to regrow hair.You may need to use this product 2 times a day for a least 4 months before you see results. The amount of hair regrowth is different for each person.

The product will not work for everyone.

STOP USE

Chest pain, rapid heart beat faintness,or dizziness occurs.
Sudden, unexplaind weight gain occurs.
Your hands or feet swell.
Scalp irritation or redness occurs.
You get unwanted facial hair growth.
You do not see hair regrowth in 4 months.

KEEP OUT OF REACH OF CHILDREN

lf swallowed, get medical help or contact a poison control center right away.

DOSAGE AND ADMINISTRATION

Spray 1ml (5 sprays) twice a day.
Once in the morning and another time in the evening before bed.
Use only on fully dry hair.
Spray directly on the scalp of hair loss area.
Results can vary and take time but we recommend at least 3-5 months of usage.

STORAGE AND HANDLING

Before use, read all information on the carton.
Keep the carton. lt contains important information.
Store at controlled room temperature 20 to 25°C (68 to 77°F).
Contents under pressure. Do not puncture or incinerate the container.
Do not expose to heat or store at temperature above 120°F (49°C)

INACTIVE INGREDIENT

WATER
Glycerin
Butylene Glycol
Alcohol
Caffeine
Biton